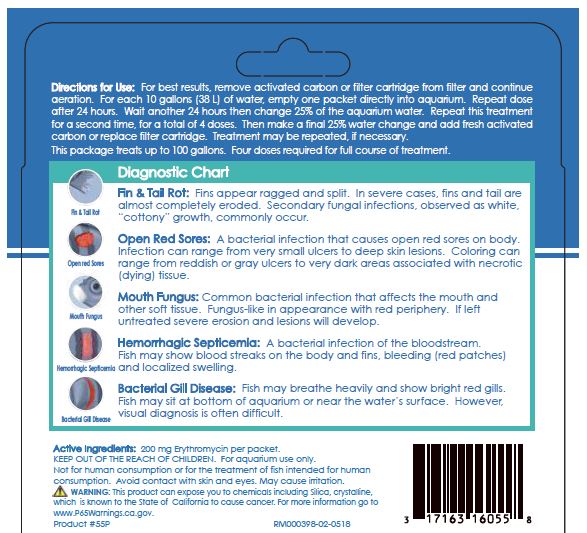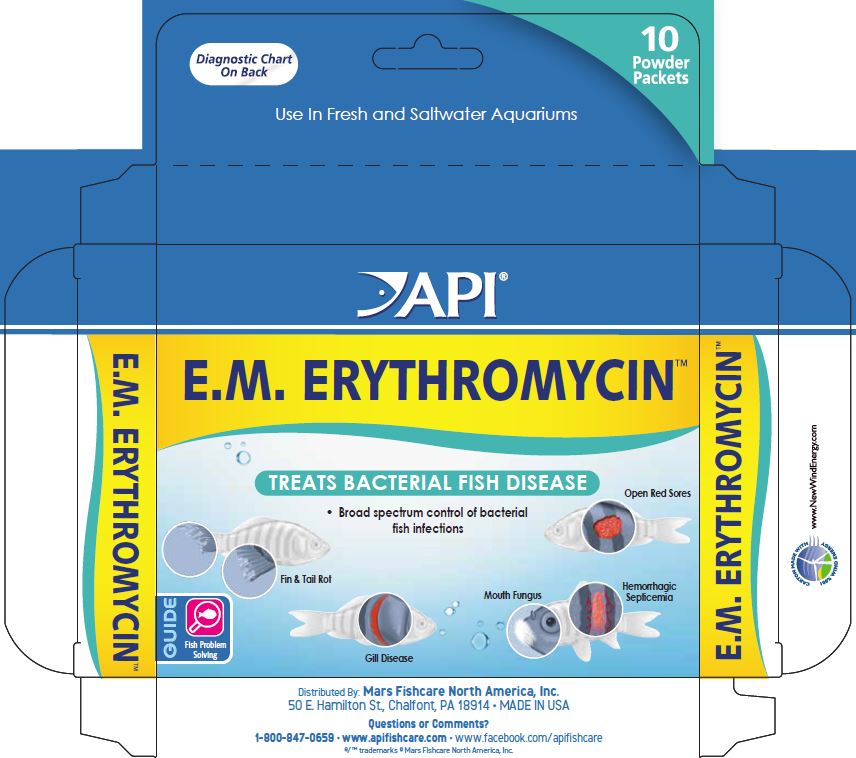 DRUG LABEL: API E.M. Erythromycin
NDC: 17163-055 | Form: POWDER
Manufacturer: MARS FISHCARE NORTH AMERICA, INC.
Category: animal | Type: OTC ANIMAL DRUG LABEL
Date: 20211229

ACTIVE INGREDIENTS: ERYTHROMYCIN 200 mg/2 g

Drug Label

Active Ingredients: 200 mg Erythromycin per packet.

DOSAGE AND ADMINISTRATION

Directions for Use:

For best results, remove activated carbon or filter cartridge from filter and continue operation.

For each 10 gallons (38 L) of water, empty one packet directly into aquarium.

Repeat does after 24 hours.

Wait another 24 hours then change 25% of the aquarium water.

Repeat this treatment for a second time, for a total of 4 doses.

Then make a final 25% water change and add fresh activated carbon or replace filter cartridge.

Treatment may be repeated, if necessary.

This package treats up to 100 gallons.

Four doses required for full course of treatment.

INDICATIONS AND USAGE

Diagnostic Chart

Fin and Tail Rot:

Fins appear ragged and split. In severe cases, fins and tails are almost completely eroded. Secondary fungal infections, observed as white, "cottony" growth, commonly occur.

Open Red Sores:

A bacterial infection that causes open red sores on body. Infection can range from very small ulcers to deep skin lesions. Coloring can range from reddish or gray ulcers to very dark areas associated with necrotic (dying) tissue.

Mouth Fungus:

Common bacterial infection that affects the mouth and other soft tissue. Fungus-like in appearance with red periphery. If left untreated severe erosion and lesions will develop

Hemorrhagic Septicemia:

A bacterial infection of the bloodstream. Fish may show blood streaks on the body and fins, bleeding (red patches) and localized swelling.

Bacterial Gill Disease:

Fish may breathe heavily and show bright red gills. Fish may sit at bottom of aquarium or near the water's surface. However, visual diagnosis is often difficult.

KEEP OUT OF REACH OF CHILDREN.

For aquarium use only.

Not for human consumption or for the treatment of fish intended for human consumption.

Avoid contact with skin and eyes.

May cause irritation.

! WARNING:

This product can expose you to chemicals including Silica, crystalline, which is known to the State of California to cause cancer.

For more information go to www.P65Warnings.ca.gov.

PACKAGE LABEL

Diagnostic Chart

On Back

10

Powder

Packets

Use In Fresh and Saltwater Aquariums

API

E.M. ERYTHROMYCIN

TREATS BACTERIAL FISH DISEASE

Broad spectrum control of bacterial

fish infections

Open Red Sores

Fin and Tail Rot

Mouth Fungus

Hemorrhagic Septicemia

Gill Disease

GUIDE

Fish Problem

Solving